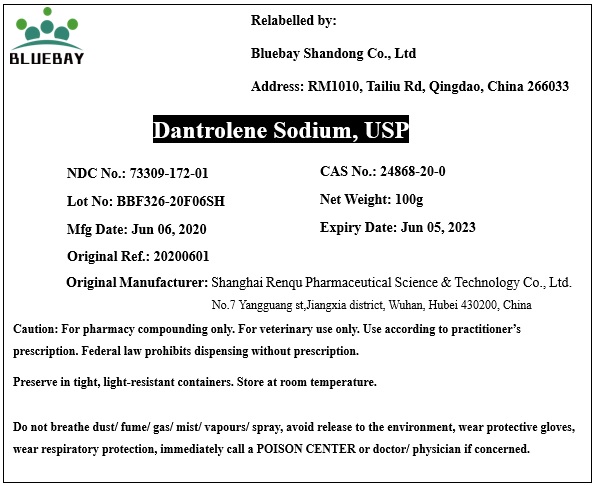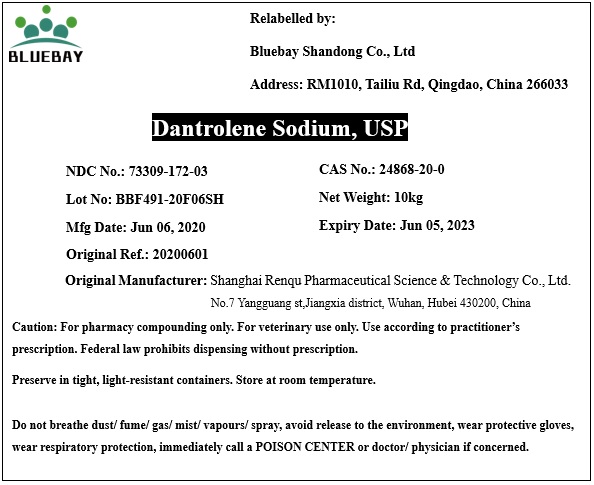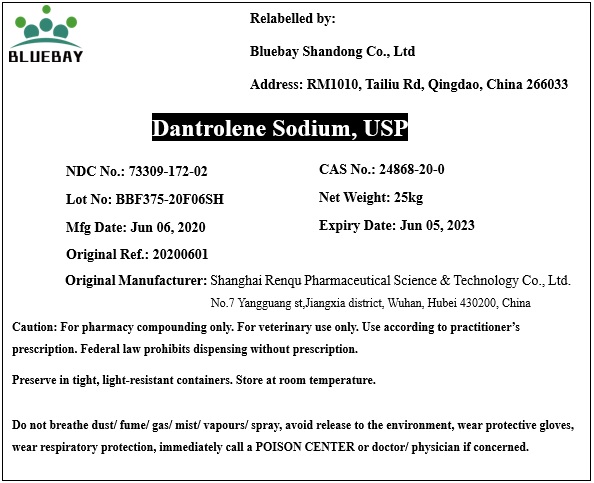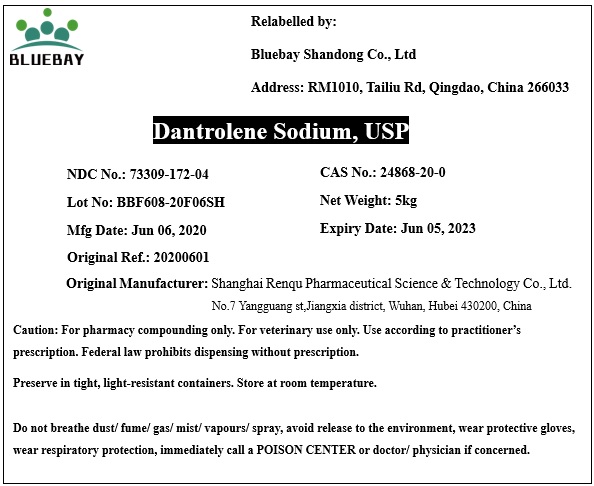 DRUG LABEL: Dantrolene Sodium
NDC: 73309-172 | Form: POWDER
Manufacturer: BLUEBAY SHANDONG CO.,LTD
Category: other | Type: BULK INGREDIENT
Date: 20201229

ACTIVE INGREDIENTS: DANTROLENE SODIUM 1 g/1 g

Dantrolene Sodium